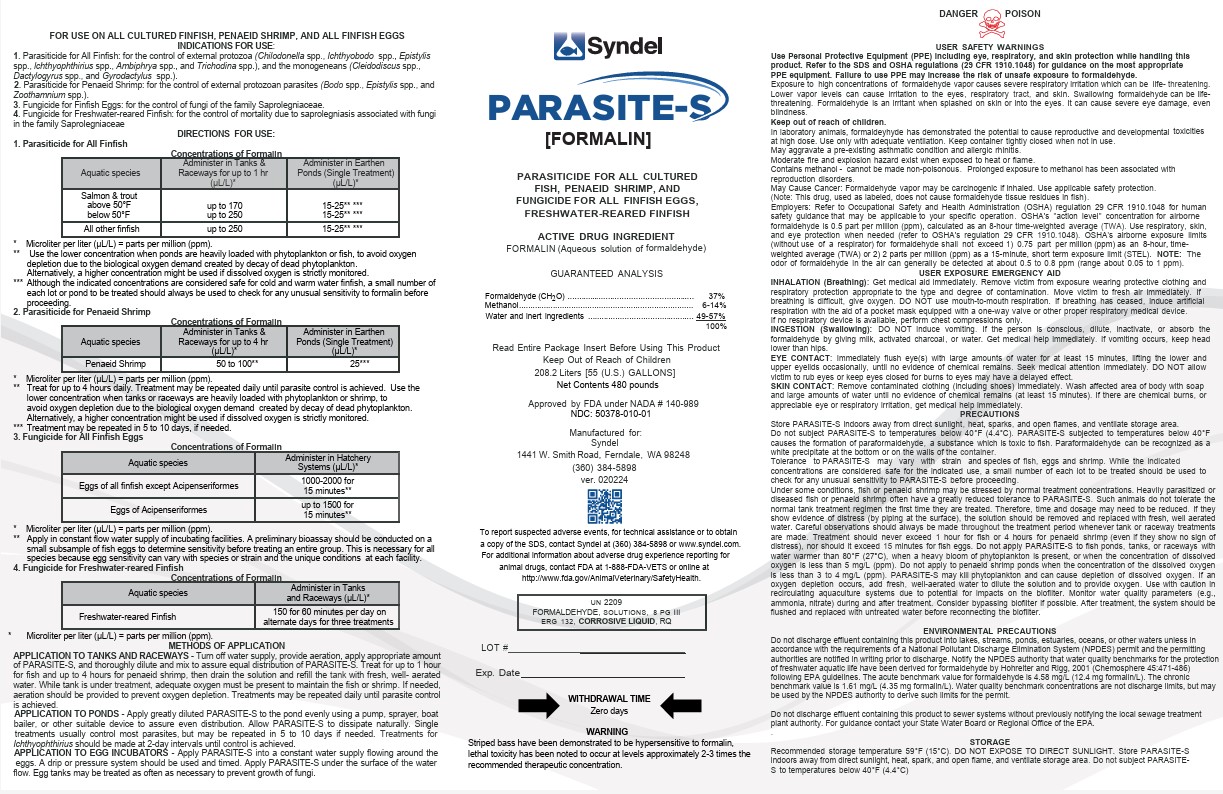 DRUG LABEL: Parasite-S
NDC: 50378-010 | Form: LIQUID
Manufacturer: Western Chemical Inc.
Category: animal | Type: OTC ANIMAL DRUG LABEL
Date: 20250225

ACTIVE INGREDIENTS: Formaldehyde 370 g/1 L
INACTIVE INGREDIENTS: Methyl alcohol 120 g/1 L; Water 510 g/1 L

PARASITE-S
Formalin (aqueous formaldehyde solution)
For control of External Protozoa and Monogenetic Trematodes on all Finfish and External Protozoans on Penaeid Shrimp; and for control of Fungi on all Finfish eggs and Freshwater-reared Finfish

DESCRIPTION

PARASITE-S is the aqueous solution of formaldehyde gas (this is equivalent to formalin 37% or
37grams of formaldehyde in 100mLof solution). U.S.P. grade PARASITE-S contains not less than
37% (by weight) of formaldehyde gas per weight of water and 6 to 14% methanol. In solution, formaldehyde
is present chiefly as HO(CH20)H. Its molecular weight is 30.93. PARASITE-S is readily
miscible with water, methanol, and ethanol and is slightly soluble in ether. It is a clear, colorless
liquid (Heyden Newport Chemical Corporation, 1961).

FISH AND SHRIMP TOXICITY STUDIES

The toxicity of PARASITE-S was measured by standard methods in laboratory bioassays with
rainbow trout, Atlantic salmon, lake trout, black bullhead, channel catfish, green sunfish, bluegill,
smallmouth bass, largemouth bass and striped bass. The 3,6,24 and 96-hour LC50 (lethal
concentration for 50% of the animals) values for trout range from 1,230 to 100 μL/L (455 to 37 ppm
formaldehyde); for catfish, from 495 to 65.8 μL/L (183 to 24 ppm formaldehyde); for bluegill,
from 1,230 to 100 μL/L (455 to 37 ppm formaldehyde); for catfish, from 495 to 65.8 μL/L (183 to 24 ppm formaldehyde);
for bluegill, from 2,290 to 100 μL/L (847 to 37 ppm formaldehyde); for largemouth bass,
the values for 6 to 96-hour LC50 range from 1,030 to 143 μL/L (381 to 53 ppm formaldehyde) (Bill et al. 1977)
and for striped bass the values for 6 to 96-hour LC50 range from 940 to 30 μL/L (347 to 11 ppm formaldehyde)
(Bills, Marking and Howe-1993). The 24, 48, 72 and 96 hour LC50 values for penaeid shrimp range
from 712 to 250 µL/L (ppm) (Johnson. 1974 and Williams, 1980).

INDICATIONS FOR USE

1. Parasiticide for Finfish: for the control of external protozoa (Chilodonella spp., Ichthyobodo spp., Epistylis spp., Ichthyophthirius spp.,Ambiphrya spp. and Trichodina spp.), and the monogenetic trematode parasites (Cleidodiscus spp., Dactylogyrus spp., and Gyrodactylus spp.).

2. Parasiticide for Penaeld Shrimp: for the control of external protozoan parasites (Bodo spp., Epistylis spp., and Zoothamnium spp.).

3. Fungicide for Finflsh Eggs: for the control of fungi of the family Saprolegniaceae.

4. Fungicide for Freshwater-reared Finfish: for the control of mortality due to saprolegniasis associated with fungi in the family Saprolegniaceae.

DIRECTIONS FOR USE

1. Parasiticide for Finfish

Concentrations of Formalin

Aquatic Species | Administer in Tanks and Raceways for up to 1 hr (µL/L)* | Administer in Earthen Ponds (Single Treatment) (µL/L)*
Salmon and Trout | Up to 170 | 15-25** ***
Above 50
Below 50 | Up to 250 | 15-25** ***
All other Finfish | Up to 250 | 15-25** ***

*Microliter per liter *(µL/L) = parts per million (ppm)

** use the lower concentration when ponds are heavily loaded with phytoplankton or fish, to avoid oygen depletion due to the biological oxygen demand created by the decay of dead phytoplankton. Although the indicated concentrations might be used if strictly monitored.

*** Although the indicated concentrations are considered safe for cold and warm water finfish, a small number of each lot of pond to be treated should always be used to check for any unusual sensitivity to formalin before proceeding.

2. Parasiticide for Penaeld Shrimp

Concentrations of Formalin
Aquatic Species | Administer in Tanks and Raceways for up to 4 hr (µL/L)* | Administer in Eartehn Ponds (Single Treatment) (µL/L)*
Penaeid Shrimp | 50 to 100 ** | 25***

* Microliter per liter (L/L) = parts per million (ppm).
** Treat for up to 4 hours daily. Treatment may be repeated daily until parasite control is achieved.
Use the lower concentration when ponds, tanks or raceways are heavily loaded with phytoplankton,
or shrimp, to avoid oxygen depletion due to the biological oxygen demand created by
decay of dead phytoplankton. Alternatively, a higher concentration might be used if dissolved
oxygen is strictly monitored.
*** Treatment may be repeated in 5 to 10 days, if needed

3. Fungicide for All Finfish Eggs

Concentrations of Formalin
Aquatic Species | Administer in Hatchery Systems (µL/L)*
Eggs of all finfish except Acipenseriformes | 1000-2000 for 15 minutes **
Eggs of Acipenseriformes | Up to 1500 for 15 minutes **

* Microliter per liter (µL/L) = parts per million (ppm)

** Apply in constant flow water supply of incubating facilities. A preliminary bioassay should be conducted on a small subsample of fish eggs to determine sensitivity before treating an entire group. This is necessary for all species because egg sensitivity can vary with species or strain and the unique conditions at each facility.

4. Fungicide for Freshwater-reared Finfish

Concentrations of Formalin
Aquatic Species | Administer in Tanks and Raceways (µL/L)*
Freshwater-reared Finfish | 150 for 60 minutes per day on alternate days for three treatments

*Microliter per Liter (µL/L) = parts per million (ppm)

METHODS OF APPLICATION

APPLICATION TO TANKS AND RACEWAYS -Turn off water supply, provide aeration, apply
appropriate amount of PARASITE-S, and thoroughly dilute and mix to assure equal distribution of
PARASITE-S. Treat for up to 1 hour for fish and up to 4 hours for penaeid shrimp, then drain the
solution and refill the tank with fresh, well-aerated water. While tank is under treatment, adequate
oxygen must be present to maintain the fish or shrimp. If needed. aeration should be provided to
prevent oxygen depletion. Treatments may be repeated daily until parasite control is achieved.
APPLICATION TO PONDS - Apply greatly diluted PARASITE-S to the pond evenly using a pump,
sprayer, boat bailer, or other suitable device to assure even distribution. Allow PARASITE-S to dissipate
naturally. Single treatments usually control most parasites, but may be repeated in 5 to 10 days if
needed. Treatments for Ichthyophthirius should be made at 2-day intervals until control is achieved.
APPLICATION TO EGG INCUBATORS - Apply PARASITE-S into a constant water supply flowing
around the eggs. A drip or pressure system should be used and timed. Apply PARASITE-S under
the surface of the water flow.

WARNINGS

WITHDRAWAL TIME
Zero days.

Warning

Striped bass have been demonstrated to be hypersensitive to formalin; lethal toxicity has been
noted to occur at levels approximately 2-3 times the recommended therapeutic concentration.

USER SAFETY WARNINGS

DANGER POISON
USER SAFETY WARNINGS

Use Personal Protective Equipment(PPE) including eye, respiratory, and skin protection while handling this product. Refer to SDS and OSHA regulations(29 CFR 1910.1048) for guidance on the most appreciate PPE equipment. Failure to use PPE may increase the risk of unsafe exposure to formaldehyde.

Exposure to high concentrations of formaldehyde vapor causes severe respiratory irritation
which can be life-threatening. Lower vapor levels can cause irritation to the eyes, respiratory
tract, and skin. Swallowing formaldehyde can be life-threatening. Formaldehyde is an irritant
when splashed on skin or Into the eyes. It can cause severe eye damage, even blindness.

Keep out of reach of children.

In laboratory animals, formaldehyde has demonstrated the potential to cause reproductive and developmental toxicities at high dose.

Use only with adequate ventilation.

Keep container tightly closed when not in use.

May aggravate a pre-existing asthmatic condition and allergic rhinitis.

Moderate fire and explosion hazard exists when exposed to heat or flame.

Contains methanol - cannot be made non-poisonous. Prolonged exposure to methanol has
been associated with reproduction disorders.

Potential Cancer Hazard: Formaldehyde vapor may be carcinogenic if inhaled. Use applicable
safety protection. (Note: This drug, used as labeled, does not cause formaldehyde
tissue residues in fish).

Employers: Refer to Occupational Safety and Health Administration (OSHA) regulation 29
CFR 1910.1048 for human safety guidance that may be applicable to your specific operation.
OSHA’s “action level” concentration for airborne formaldehyde is 0.5 part per million
(ppm), calculated as an 8 hour time-weighted average (TWA). Use respiratory, skin, and eye
protection when needed (refer to OSHA’s regulation 29 CFR 1910.1048). OSHA’s airborne
exposure limits (without use of a respirator) for formaldehyde shall not exceed 1) 0.75 part
per million (ppm) as an 8-hour, time-weighted average (TWA) or 2) 2 parts per million (ppm)
as a 15-minute, short term exposure limit (STEL). NOTE: The odor of formaldehyde in the air
can generally be detected at about 0.5 to 0.8 ppm (range about 0.05 to 1 ppm).

USER EXPOSURE EMERGENCY AID

INHALATION (Breathing): Get medical aid immediately. Remove victim from exposure
wearing protective clothing and respiratory protection appropriate to the type and degree of
contamination. Move victim to fresh air immediately. If breathing is difficult, give oxygen. DO
NOT use mouth-to-mouth respiration. If breathing has ceased, induce artificial respiration
with the aid of a pocket mask equipped with a one-way valve or other proper respiratory
medical device.

INGESTION (Swallowing): DO NOT induce vomiting. If the person is conscious, dilute,
inactivate, or absorb the formaldehyde by giving milk, activated charcoal, or water. Get
medical help immediately. If vomiting occurs, keep head lower than hips.

EYE CONTACT: Immediately flush eye(s) with large amounts of water for at least 15 minutes,
lifting the lower and upper eyelids occasionally, until no evidence of chemical remains.
Seek medical attention immediately. DO NOT allow victim to rub eyes or keep eyes closed
for burns to eyes may have a delayed effect.

SKIN CONTACT: Remove contaminated clothing (including shoes) immediately. Wash affected
area of body with soap and large amounts of water until no evidence of chemical
remains (at least 15 minutes). If there are chemical burns, or appreciable eye or respiratory
irritation, get medical help immediately.

PRECAUTIONS

Store PARASITE-S indoors away from direct sunlight, heat, sparks, and open flames, and ventilate storage area.

Do not subject PARASITE-S to temperatures below 40°F (4.4°C). PARASITE-S subjected to temperatures below 40°F causes the formation of paraformaldehyde, a substance which is toxic to fish. Paraformaldehyde can be recognized as a white precipitate at the bottom or on the walls of the container.

Tolerance to PARASITE-S may vary with strain and species of fish, eggs and shrimp. While the indicated
concentrations are considered safe for the indicated use, a small number of each lot to be treated should be used to check for any unusual sensitivity to PARASITE-S before proceeding.

Under some conditions, fish or penaeid shrimp may be stressed by normal treatment concentrations. Heavily parasitized or diseased fish or penaeid shrimp often have a greatly reduced tolerance to PARASITE-S. Such animals do not tolerate the normal tank treatment regimen the first time they are treated. Therefore, time and dosage may need to be reduced. If they show evidence of distress (by piping at the surface), the solution should be removed and replaced with fresh, well aerated water. Careful observations should always be made throughout the treatment period whenever tank or raceway treatments are made. Treatment should never exceed 1 hour for fish or 4 hours for penaeid shrimp (even if they show no sign of distress), nor should it exceed 15 minutes for fish eggs.

Do not apply PARASITE-S to fish ponds, tanks, or raceways with water warmer than 80°F (27°C), when a heavy bloom of phytoplankton is present, or when the concentration of dissolved oxygen is less than 5 mg/L (ppm). Do not apply to penaeid shrimp ponds when the concentration of the dissolved oxygen is less than 3 to 4 mg/L (ppm). PARASITE-S may kill phytoplankton and can cause depletion of dissolved oxygen. If an oxygen depletion occurs, add fresh, well-aerated water to dilute the solution and to provide oxygen.

Use with caution in recirculating aquaculture systems due to potential for impacts on the biofilter. Monitor water quality parameters (e.g., ammonia, nitrate) during and after treatment. Consider bypassing biofilter if possible. After treatment, the system should be flushed and replaced with untreated water before reconnecting the biofilter.

ENVIRONMENTAL PRECAUTIONS

Do not discharge effluent containing this product into lakes, streams, ponds, estuaries, oceans, or other waters unless in accordance with the requirements of a National Pollutant Discharge Elimination System (NPDES) permit and the permitting authorities are notified in writing prior to discharge. Notify the NPDES authority that water quality benchmarks for the protection of freshwater aquatic life have been derived for formaldehyde by Hohreiter and Rigg, 2001 (Chemosphere 45:471-486) following EPA guidelines. The acute benchmark value for formaldehyde is 4.58 mg/L (12.4 mg formalin/L). The chronic benchmark value is 1.61 mg/L (4.35 mg formalin/L). Water quality benchmark concentrations are not discharge limits, but may be used by the NPDES authority to derive such limits for the permit.

Do not discharge effluent containing this product to sewer systems without previously notifying the local sewage treatment plant authority. For guidance contact your State Water Board or Regional Office of the EPA.

STORAGE

Recommended storage temperature 59°F (15°C). DO NOT EXPOSE TO DIRECT SUNLIGHT.
Store PARASITE-S indoors away from direct sunlight, heat, spark, and open flame,
and ventilate storage area. Do not subject PARASITE-S to temperatures below 40°F (4.4°C).

To report suspected adverse events, for technical assistance, or to obtain a copy of the SDS, contact Syndel at (360) 384-5898 or www.syndel.com. For additional information about adverse drug experience reporting for animal drugs, contact FDA at 1-888-FDA-VETS or online at http://www.fda.gov/AnimalVeterinary/SafetyHealth

Manufactured for:
Syndel
1441 W. Smith Road, Ferndale, WA 98248
(360) 384-5898
Ver. 030519

Approved by FDA under NADA# 140-989